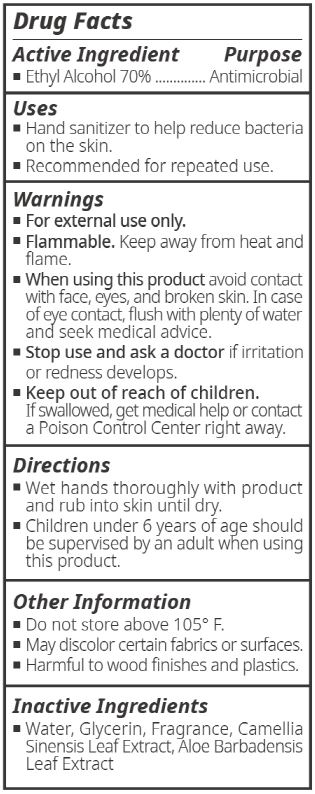 DRUG LABEL: CHOBS-READY TO HAND SANITIZER
NDC: 74122-0012 | Form: SPRAY
Manufacturer: CH Harmony Co., Ltd.
Category: otc | Type: HUMAN OTC DRUG LABEL
Date: 20200402

ACTIVE INGREDIENTS: ALCOHOL 66.5 mL/95 mL
INACTIVE INGREDIENTS: WATER

CH Harmony Co., Ltd. - CHOBS-READY TO HAND SANITIZER

ACTIVE INGREDIENT

Alcohol

INACTIVE INGREDIENT

water, glycerin, camellia sinensis leaf extract, aloe barbadensis leaf extract, frgrance

PURPOSE

Antiseptic

keep out of reach of the children

INDICATIONS AND USAGE

Wet hands thoroughly with product and rub into skin until dry.

Children under 6 years of age should be supervised by an adult when using this product.

WARNINGS

For external use only.

Flammable.

Keep away from fire or flame.

DOSAGE AND ADMINISTRATION

for external use only